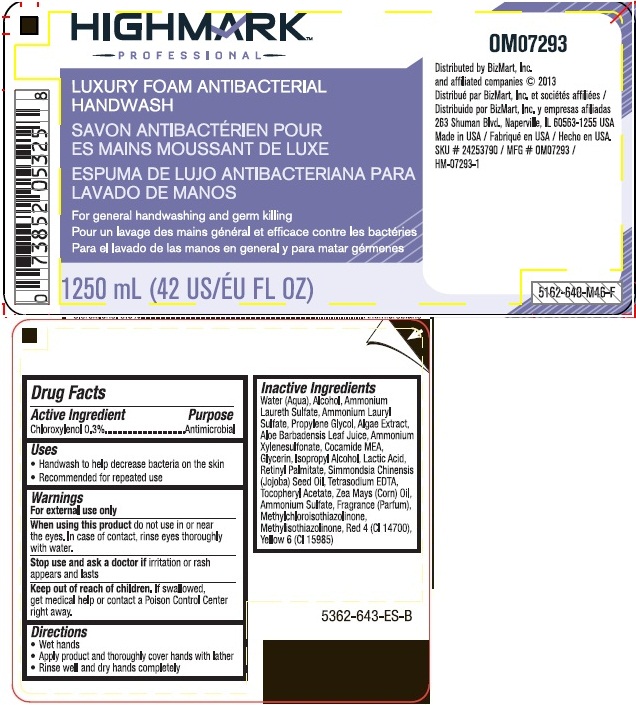 DRUG LABEL: Highmark Professional Luxury Foam Antibacterial Handwash
NDC: 61139-512 | Form: LIQUID
Manufacturer: Office Max, Inc.
Category: otc | Type: HUMAN OTC DRUG LABEL
Date: 20131122

ACTIVE INGREDIENTS: CHLOROXYLENOL 0.003 mg/1 mL
INACTIVE INGREDIENTS: WATER; ALCOHOL; AMMONIUM LAURETH-2 SULFATE; AMMONIUM LAURYL SULFATE; PROPYLENE GLYCOL; ALOE VERA LEAF; AMMONIUM XYLENESULFONATE; COCO MONOETHANOLAMIDE; GLYCERIN; ISOPROPYL ALCOHOL; LACTIC ACID; VITAMIN A PALMITATE; JOJOBA OIL; EDETATE SODIUM; .ALPHA.-TOCOPHEROL ACETATE, D-; CORN OIL; AMMONIUM SULFATE; METHYLCHLOROISOTHIAZOLINONE; METHYLISOTHIAZOLINONE; FD&C RED NO. 4; FD&C YELLOW NO. 6

Highmark Professional Luxury Foam Antibacterial Handwash

Active ingredient

Chloroxylenol 0.3%

Purpose

Antimicrobial

Use

Handwash to help decrease bacteria on the skin.

Recommended for repeated use.

Directions

Wet hands

Apply product and thoroughly cover hands with lather

Rinse well and dry hands completely

Inactive ingredients

Water (Aqua), Alcohol, Ammonium Laureth Sulfate, Ammonium Lauryl Sulfate, Propylene Glycol, Algae Extract, Aloe Barbadensis Leaf Juice, Ammonium Xylenesulfonate, Cocamide MEA, Glycerin, Isopropyl Alcohol, Lactic-Acid, Retinyl Palmitate, Simmondsia Chinensis (Jojoba) Seed Oil, Tetrasodium EDTA, Tocopheryl Acetate, Zea Mays (Corn) Oil, Ammonium Sulfate, Fragrance (Parfum) Methylchloroisothiazolinone, Methylisothiazolinone, Red 4 (CI 14700), Yellow 6 (CI 15985)

Package Label

For general hand washing and germ killing

Warnings

For external use only

When using this product do not use in or near the eyes. In case of contact, rinse eyes thoroughly with water.

Stop use and ask a doctor if irritation or rash appears and lasts

Keep out of reach of children. If swallowed, get medical help or contact a Poison Control Center right away.